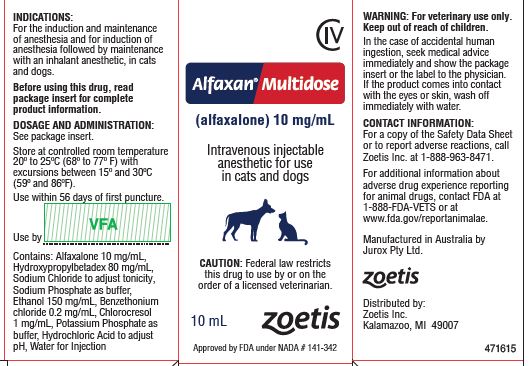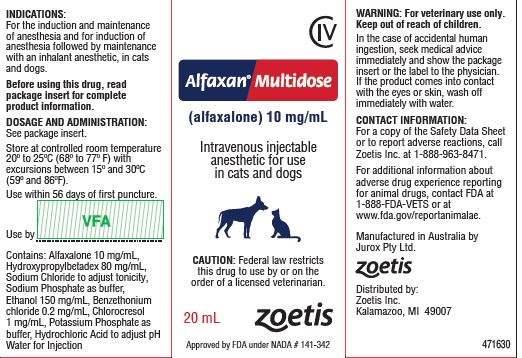 DRUG LABEL: ALFAXAN
NDC: 54771-6696 | Form: INJECTION, SOLUTION
Manufacturer: Zoetis Inc.
Category: animal | Type: PRESCRIPTION ANIMAL DRUG LABEL
Date: 20230516
DEA Schedule: CIV

ACTIVE INGREDIENTS: ALFAXALONE 10 mg/1 mL
INACTIVE INGREDIENTS: HYDROXYPROPYLBETADEX (0.58-0.68 MS) 80 mg/1 mL; SODIUM CHLORIDE; SODIUM PHOSPHATE, DIBASIC, ANHYDROUS; ALCOHOL 150 mg/1 mL; BENZETHONIUM CHLORIDE 0.2 mg/1 mL; CHLOROCRESOL 1 mg/1 mL; POTASSIUM PHOSPHATE, MONOBASIC; HYDROCHLORIC ACID

ALFAXAN MULTIDOSE

For Animal Use Only
Alfaxan® Multidose CIV
(alfaxalone) 10 mg/mL
Intravenous injectable anesthetic for use in cats and dogs.

CAUTION

Federal law restricts this drug to use by or on the order of a licensed veterinarian.

DESCRIPTION

ALFAXAN MULTIDOSE (alfaxalone) is a neuroactive steroid molecule with properties of a general anesthetic. Alfaxalone is chemically described as 3-α-hydroxy-5-α-pregnane-11, 20-dione, and has a molecular weight 332.5. The primary mechanism for the anesthetic action of alfaxalone is modulation of neuronal cell membrane chloride ion transport, induced by binding of alfaxalone to GABAA (gamma-aminobutyric acid) cell surface receptors.

INDICATIONS

ALFAXAN MULTIDOSE is indicated for the induction and maintenance of anesthesia and for induction of anesthesia followed by maintenance with an inhalant anesthetic, in cats and dogs.

DOSAGE AND ADMINISTRATION

Administer by intravenous injection only. For induction, administer ALFAXAN MULTIDOSE over approximately 60 seconds or until clinical signs show the onset of anesthesia, titrating administration against the response of the patient. Rapid administration of ALFAXAN MULTIDOSE may be associated with an increased incidence of cardiorespiratory depression or apnea. Apnea can occur following induction or after the administration of maintenance boluses of ALFAXAN MULTIDOSE. The use of preanesthetics may reduce the ALFAXAN MULTIDOSE induction dose. The choice and the amount of phenothiazine, alpha2-adrenoreceptor agonist, benzodiazepine or opioid will influence the response of the patient to an induction dose of ALFAXAN MULTIDOSE.

When using ALFAXAN MULTIDOSE, patients should be continuously monitored, and facilities for the maintenance of a patent airway, artificial ventilation, and oxygen supplementation must be immediately available.

ALFAXAN MULTIDOSE contains preservatives. Use within 56 days of first puncture. Any unused ALFAXAN MULTIDOSE remaining after 56 days should be discarded.

ALFAXAN MULTIDOSE should not be mixed with other therapeutic agents prior to administration.

CATS

Induction of general anesthesia in cats: Induction dose guidelines are based on data from the field study (see EFFECTIVENESS) and range between 2.2 - 9.7 mg/kg for cats that did not receive a preanesthetic, and between 1.0 - 10.8 mg/kg for cats that received a preanesthetic. The alfaxalone induction dose in the field study was reduced by 10 - 43%, depending on the combination of preanesthetics (dose sparing effect). Dose sparing of ALFAXAN MULTIDOSE will depend on the potency, dose, and time of administration of the various preanesthetics that are used prior to induction. To avoid anesthetic overdose, titrate the administration of ALFAXAN MULTIDOSE against the response of the patient.

Anesthesia is usually observed within 60 seconds after the start of injection, and permits intubation within 1 - 2 minutes, irrespective of preanesthetic. The duration of anesthesia from a single induction dose ranges between 15 - 30 minutes in the unpreanesthetized cat. If a preanesthetic is used, anesthetic duration may be longer, depending on the class and dose of preanesthetic. Individual anesthesia times vary.

Examples from the field study of average induction doses (and ranges) for cats that received various preanesthetics are presented as dosing guidelines in the table. The table is for guidance only. Draw up the maximum expected target dose and administer to effect. The actual induction dose should be based on patient response.

Alfaxalone Induction Dose Guidelines: CATS
Preanesthetic | Average alfaxalone induction dose (and range) in mg/kg | Number of cats
No preanesthetic | 4.0 (2.2-9.7) | 33
Opioid + phenothiazine | 3.2 (1.1-10.8) | 96
Benzodiazepine + phenothiazine | 3.6 (1.5-7.1) | 23
Benzodiazepine + opioid + phenothiazine | 2.3 (1.2-5.0) | 26
Alpha2-adrenergic agonist with/without phenothiazine | 3.6 (1.1-5.0) | 15
Alpha2-adrenergic agonist + phenothiazine with/without benzodiazepine or opioid | 2.9 (1.0-3.9) | 11

Additional doses of ALFAXAN MULTIDOSE similar to those used for maintenance (1.1 - 1.5 mg/kg) may be administered to facilitate intubation.

Maintenance of general anesthesia in cats: Following induction of anesthesia with ALFAXAN MULTIDOSE and intubation, anesthesia may be maintained using intermittent ALFAXAN MULTIDOSE intravenous boluses or an inhalant anesthetic agent. A maintenance bolus containing 1.1 - 1.3 mg/kg provides an additional 7 - 8 minutes of anesthesia in preanesthetized cats. A dose of 1.4 - 1.5 mg/kg provides an additional 3 - 5 minutes anesthesia in unpreanesthetized cats. Clinical response may vary, and is determined by the dose, rate of administration, and frequency of maintenance injections.

ALFAXAN MULTIDOSE maintenance dose sparing is greater in cats that receive a preanesthetic. Examples from the field study of maintenance doses for preanesthetized and unpreanesthetized cats are presented as guidelines in the table. Maintenance dose and frequency should be based on the response of the individual patient.

Alfaxalone Maintenance Dose Guidelines: CATS
Dose and Duration | Preanesthetized Cats | Unpreanesthetized Cats
Maintenance anesthesia doses | 1.1 - 1.3 mg/kg | 1.4 - 1.5 mg/kg
Mean duration of anesthesia | 7-8 minutes | 3 - 5 minutes

In the field study, recovery times (extubation to head lift) following alfaxalone maintenance anesthesia averaged 15 minutes in cats that did not receive a preanesthetic, and 17 minutes in preanesthetized cats.

Inhalant anesthetic maintenance of general anesthesia in cats: Additional low doses of ALFAXAN MULTIDOSE, similar to a maintenance dose, may be required to facilitate the transition to inhalant maintenance anesthesia.

DOGS

Induction of general anesthesia in dogs: Induction dose guidelines are based on data from the field study (see EFFECTIVENESS) and range between 1.5 - 4.5 mg/kg for dogs that did not receive a preanesthetic, and between 0.2 - 3.5 mg/kg for dogs that received a preanesthetic. The alfaxalone induction dose in the field study was reduced by 23 - 50% depending on the combination of preanesthetics (dose sparing effect). Dose sparing of ALFAXAN MULTIDOSE will depend on the potency, dose, and time of administration of the various preanesthetics that are used prior to induction. To avoid anesthetic overdose, titrate the administration of ALFAXAN MULTIDOSE against the response of the patient. In the field study, the use of a preanesthetic appeared to decrease the occurrence of apnea following alfaxalone induction in dogs.

In dogs, ALFAXAN MULTIDOSE usually produces recumbence within 60 seconds after the start of injection, and permits intubation within 1 - 2 minutes, irrespective of preanesthetic. The duration of anesthesia from a single induction dose is approximately 5 - 10 minutes in the unpreanesthetized dog. If a preanesthetic is used, anesthetic duration may be longer, depending on the class and dose of preanesthetic. Individual anesthesia times vary.

Examples from the field study of average induction doses (and ranges) for dogs that received various preanesthetics are presented as dosing guidelines in the table. The table is for guidance only. Draw up the maximum expected target dose and administer to effect. The actual induction dose should be based on patient response.

Alfaxalone Induction Dose Guidelines: DOGS
Preanesthetic | Average alfaxalone induction dose (and range) in mg/kg | Number of dogs
No preanesthetic | 2.2 (1.5 - 4.5) | 17
Benzodiazepine + opioid + acepromazine | 1.7 (0.9 - 3.5) | 39
Opioid + acepromazine | 1.6 (0.6 - 3.5) | 80
Alpha2-agonist | 1.1 (0.21 - 2.00) | 9

Additional doses of ALFAXAN MULTIDOSE similar to those used for maintenance (1.2 - 2.2 mg/kg) may be administered to facilitate intubation.

Maintenance of general anesthesia in dogs: Following induction of anesthesia with ALFAXAN MULTIDOSE and intubation, anesthesia may be maintained using intermittent ALFAXAN MULTIDOSE intravenous boluses or an inhalant anesthetic agent. A maintenance bolus containing 1.2 - 1.4 mg/kg provides an additional 6 - 8 minutes anesthesia in preanesthetized dogs. A dose of 1.5 - 2.2 mg/kg provides an additional 6 - 8 minutes of anesthesia in unpreanesthetized dogs. Clinical response may vary, and is determined by the dose, rate of administration, and frequency of maintenance injections.

ALFAXAN MULTIDOSE maintenance dose sparing is greater in dogs that receive a preanesthetic. Examples from the field study of maintenance doses for preanesthetized and unpreanesthetized dogs are presented as guidelines in the table. Maintenance dose and frequency should be based on the response of the individual patient.

Alfaxalone Maintenance Dose Guidelines: DOGS
Dose and Duration | Preanesthetized Dogs | Unpreanesthetized Dogs
Maintenance anesthesia doses | 1.2 - 1.4 mg/kg | 1.5 - 2.2 mg/kg
Mean duration of anesthesia | 6 - 8 minutes | 6 - 8 minutes

In the field study, recovery times (extubation to head lift) following alfaxalone maintenance anesthesia averaged 22 minutes in dogs that did not receive a preanesthetic, and 15 minutes in preanesthetized dogs.

Inhalant anesthetic maintenance of general anesthesia in dogs: Additional low doses of ALFAXAN MULTIDOSE, similar to a maintenance dose, may be required to facilitate the transition to inhalant maintenance anesthesia.

DRUG INTERACTIONS

No specific preanesthetic is either indicated or contraindicated with ALFAXAN MULTIDOSE. The necessity for and choice of preanesthetic is left to the discretion of the veterinarian. Preanesthetic doses may be lower than the label directions for their use as a single medication. ALFAXAN MULTIDOSE is compatible with benzodiazepines, opioids, alpha2-agonists, and phenothiazines as commonly used in surgical practice.

In the field study, alfaxalone was used safely in cats and dogs that received frequently used veterinary products, including antibiotics, anticholinergics, vaccines, steroids, and dewormers.

CONTRAINDICATIONS

ALFAXAN MULTIDOSE is contraindicated in cats and dogs with a known sensitivity to ALFAXAN MULTIDOSE or its components, or when general anesthesia and/or sedation are contraindicated.

WARNINGS

Animal safety: When using ALFAXAN MULTIDOSE, patients should be continuously monitored, and facilities for the maintenance of a patent airway, artificial ventilation, and oxygen supplementation must be immediately available.
Rapid bolus administration or anesthetic overdose may cause cardiorespiratory depression, including hypotension, apnea, hypoxia, or death. Arrhythmias may occur secondary to apnea and hypoxia. In cases of anesthetic overdose, stop ALFAXAN MULTIDOSE administration and administer treatment as indicated by the patient’s clinical signs. Cardiovascular depression should be treated with plasma expanders, pressor agents, anti-arrhythmic agents or other techniques as appropriate for the treatments of the clinical signs.
Human safety: Not for human use. Keep out of the reach of children.
ALFAXAN MULTIDOSE should be managed to prevent the risk of diversion, through such measures as restriction of access and the use of drug accountability procedures appropriate to the clinical setting.
Exercise caution to avoid accidental self-injection. Overdose is likely to cause cardiorespiratory depression (such as hypotension, bradycardia and/or apnea). Remove the individual from the source of exposure and seek medical attention. Respiratory depression should be treated by artificial ventilation and oxygen.
Avoid contact of this product with skin, eyes, and clothes. In case of contact, eyes and skin should be liberally flushed with water for 15 minutes. Consult a physician if irritation persists. In the case of accidental human ingestion, seek medical advice immediately and show the package insert or the label to the physician.
Note to physician: This product contains an injectable anesthetic.

CONTACT INFORMATION

For a copy of the Safety Data Sheet or to report adverse reactions, call Zoetis Inc. at 1-888-963-8471. For additional information about adverse drug experience reporting for animal drugs, contact FDA at 1-888-FDA-VETS or at www.fda.gov/reportanimalae.

DRUG ABUSE AND DEPENDENCE

Controlled substance: ALFAXAN MULTIDOSE contains alfaxalone a neurosteroid anesthetic and a class IV controlled substance.
Abuse: Alfaxalone is a central nervous system depressant that acts on GABA receptor associated chloride channels, similar to the mechanism of action of Schedule IV sedatives such as benzodiazepines (diazepam and midazolam), barbiturates (phenobarbital and methohexital) and fospropofol. In a drug discrimination behavioral test in rats, the effects of alfaxalone were recognized as similar to those of midazolam. These biochemical and behavioral data suggest that alfaxalone has an abuse potential similar to other Schedule IV sedatives.
Physical dependence: There are no data that assess the ability of alfaxalone to induce physical dependence. However, alfaxalone has a mechanism of action similar to the benzodiazepines and can block the behavioral responses associated with precipitated benzodiazepine withdrawal. Therefore, it is likely that alfaxalone can also produce physical dependence and withdrawal signs similar to that produced by the benzodiazepines.
Psychological dependence: The ability of alfaxalone to produce psychological dependence is unknown because there are no data on the rewarding properties of the drug from animal self-administration studies or from human abuse potential studies.

PRECAUTIONS

Rapid arousal: Careful monitoring of the patient is necessary due to possibility of rapid arousal.

Preanesthesia: Benzodiazepines may be used safely prior to ALFAXAN MULTIDOSE in the presence of other preanesthetics (see DRUG INTERACTIONS). However, when a benzodiazepine was used as the sole preanesthetic, excitation occurred in some cats and dogs during ALFAXAN MULTIDOSE anesthesia and recovery.

Apnea: Apnea may occur following administration of an induction dose, a maintenance dose or a dose administered during the transition to inhalant maintenance anesthesia, especially with higher doses and rapid administration. Endotracheal intubation, oxygen supplementation, and intermittent positive pressure ventilation (IPPV) should be administered to treat apnea and associated hypoxemia.

Blood Pressure: The myocardial depressive effects of ALFAXAN MULTIDOSE combined with the vasodilatory effects of inhalant anesthetics can be additive, resulting in hypotension. Preanesthetics may increase the anesthesia effect of ALFAXAN MULTIDOSE and result in more pronounced changes in systolic, diastolic, and mean arterial blood pressures. Transient hypertension may occur, possibly due to elevated sympathetic activity.

Body Temperature: A decrease in body temperature occurs during ALFAXAN MULTIDOSE anesthesia unless an external heat source is provided. Supplemental heat should be provided to maintain acceptable core body temperature until full recovery.

Breeding Animals: ALFAXAN MULTIDOSE has not been evaluated in pregnant, lactating, and breeding cats. Alfaxalone crosses the placenta, and as with other general anesthetic agents, the administration of ALFAXAN MULTIDOSE may be associated with neonatal depression.

Kittens and Puppies: ALFAXAN MULTIDOSE has not been evaluated in cats less than 4 weeks of age or in dogs less than 10 weeks of age.

Compromised or Debilitated Cats and Dogs: The administration of ALFAXAN MULTIDOSE to debilitated patients or patients with renal disease, hepatic disease, or cardiorespiratory disease has not been evaluated. Doses may need adjustment for geriatric or debilitated patients. Caution should be used in cats or dogs with cardiac, respiratory, renal or hepatic impairment, or in hypovolemic or debilitated cats and dogs, and geriatric animals.

Analgesia during anesthesia: Appropriate analgesia should be provided for painful procedures.

ADVERSE REACTIONS

Adverse Reactions in Cat Field Study
Adverse Reaction | Number of Catsa = 207
Hypotension (≤90 mm Hg) | 92
Tachycardia (≥ 180 bpm) | 61
Apnea (≥ 30 seconds) | 32 (of 202)
Hypertension (> 165 mm Hg) | 23
Bradypnea (RR< 10 breaths/min) | 16
Apnea (≥ 60 seconds) | 12 (of 202)
Bradycardia (≤90 beats/min) | 10
Hypothermia (<97°F) | 10
Hypoxia (SpO2 <85%) | 4
Emesis | 1
Unacceptable Anesthesia Quality | 1
aEach cat may have experienced more than one adverse reaction

Additional adverse reactions for cats included vocalization, paddling, and muscle tremors. One cat that experienced tachycardia and hypoxia during anesthesia was euthanized 3 days later due to carcinoma involving the liver, pancreas and common bile duct. The relationship of the original tachycardia during anesthesia and the carcinoma is unknown.

Adverse Reactions in Dog Field Study
Adverse Reaction | Number of Dogsa = 182
Bradypnea (RR< 10 breaths/min) | 89
Apnea (≥ 30 seconds) | 55 (of 137)
Hypertension (> 165 mm Hg) | 54
Tachycardia (≥ 180 bpm) | 49
Apnea (≥ 60 seconds) | 34 (of 137)
Hypotension (≤70 mm Hg) | 32
Hypothermia (<97°F) | 28
Bradycardia (≤70 beats/min) | 24
Hypoxia (SpO2 <85%) | 4
Lack of Effectiveness | 3
Unacceptable Anesthesia Quality | 1
Emesis | 1
aEach dog may have experienced more than one adverse reaction

Additional adverse reactions for dogs included vocalization, paddling, and muscle tremors.
To report adverse reactions or to obtain a copy of the SDS for this product call 1-888-963-8471.
For additional information about adverse drug experience reporting for animal drugs, contact FDA at 1-888-FDA-VETS or http://www.fda.gov/reportanimalae.

OVERDOSE

Rapid administration, accidental overdose, or relative overdose due to inadequate dose sparing of ALFAXAN MULTIDOSE in the presence of preanesthetics may cause cardiopulmonary depression. Respiratory arrest (apnea) may be observed. In cases of respiratory depression, stop drug administration, establish a patent airway, and initiate assisted or controlled ventilation with pure oxygen. Cardiovascular depression should be treated with plasma expanders, pressor agents, antiarrhythmic agents or other techniques as appropriate for the observed abnormality.

CLINICAL PHARMACOLOGY

ALFAXAN MULTIDOSE is a reformulation of previously approved, single-use ALFAXAN (NADA 141-342) which contained no antimicrobial preservative. The bioequivalence of ALFAXAN (unpreserved) and ALFAXAN MULTIDOSE following administration of 5 mg/kg IV was demonstrated in a two sequence, two period crossover study in 24 cats (see EFFECTIVENESS). The bioequivalence of ALFAXAN (unpreserved) and ALFAXAN MULTIDOSE following administration of 3 mg/kg IV was demonstrated in a two sequence, two period crossover study in 24 dogs (see EFFECTIVENESS).

EFFECTIVENESS

Cat bioequivalence study: The bioequivalence of ALFAXAN (unpreserved) and ALFAXAN MULTIDOSE following administration of 5 mg/kg IV was demonstrated in a two sequence, two period crossover study in 24 cats. The two products were bioequivalent because the upper and lower bounds of the 90% confidence intervals for Cmax and AUClast of ALFAXAN (unpreserved) and ALFAXAN MULTIDOSE met the bioequivalence criteria of 80 - 125%.

Table 1. Summary of bioequivalence parameters following a single IV administration of 5 mg/kg in cats of ALFAXAN (unpreserved) and ALFAXAN MULTIDOSE:
Parameter | Product | Geo LS Mean^1 | T/R* | Lower Bound^2 | Upper Bound^2
Cmax (g/mL) | ALFAXAN (unpreserved) | 8.45 | 0.97 | 91.58% | 102.38%
 | ALFAXAN MULTIDOSE | 8.18
AUClast (min*g/mL) | ALFAXAN (unpreserved) | 186.07 | 0.98 | 93.11% | 102.77%
 | ALFAXAN MULTIDOSE | 182.01

*T/R = Test/Reference = ALFAXAN MULTIDOSE/ALFAXAN (unpreserved)

^1Geometric means

^2Lower and upper 90% confidence bounds for the ratio of ALFAXAN (unpreserved) and ALFAXAN MULTIDOSE

Dog bioequivalence study: The bioequivalence of ALFAXAN (unpreserved) and ALFAXAN MULTIDOSE following administration of 3 mg/kg IV was demonstrated in a two sequence, two period crossover study in 24 dogs. The two products were bioequivalent, because the upper and lower bounds of the 90% confidence intervals for Cmax and AUClast of ALFAXAN (unpreserved) and ALFAXAN MULTIDOSE met the bioequivalence criteria of 80 - 125%.

Table 2. Summary of bioequivalence parameters following a single IV administration of 3 mg/kg in dogs of ALFAXAN (unpreserved) and ALFAXAN MULTIDOSE:
Parameter | Product | Geo LS Mean^1 | T/R* | Lower Bound^2 | Upper Bound^2
Cmax (g/mL) | ALFAXAN (unpreserved) | 4.42 | 1.07 | 100.26% | 114.57%
 | ALFAXAN MULTIDOSE | 4.74
AUClast (min*g/mL) | ALFAXAN (unpreserved) | 74.77 | 1.06 | 101.52% | 109.72%
 | ALFAXAN MULTIDOSE | 78.92

*T/R = Test/Reference = ALFAXAN MULTIDOSE/ALFAXAN (unpreserved)

^1Geometric means

^2Lower and upper 90% confidence bounds for the ratio of ALFAXAN (unpreserved) and ALFAXAN MULTIDOSE

Cat Field Study: Two hundred and seven cats of 19 breeds, between the ages of 1 month to 17 years, weighing between 0.6-9 kg, were successfully anesthetized with alfaxalone (unpreserved) for various types of surgery or procedures requiring anesthesia. Induction doses ranged between 1.0-10.8 mg/kg for cats that received preanesthetics, and between 2.2-9.7 mg/kg for unpreanesthetized cats (see DOSAGE AND ADMINISTRATION for doses by preanesthetic treatment groups). For most cats, the alfaxalone induction dose was reduced (10-43%), depending on the combination of preanesthetics (dose sparing effect). One hundred and four cats were maintained using an inhalant anesthetic; 72 cats were maintained using between 1 to 5 alfaxalone boluses. Mean alfaxalone maintenance doses ranged between 1.1-1.3 mg/kg in preanesthetized cats and 1.4-1.5 in unpreanesthetized cats. Doses were given to effect and titrated against the response of the individual patient.

All cats in the field study were intubated and received supplemental oxygen. Apnea ≥30 seconds occurred in 28 (of 169) preanesthetized cats and 4 (of 33) unpreanesthetized cats after induction with alfaxalone. Apnea continued ≥60 seconds in 9 of the 28 apneic preanesthetized cats and 3 of the 4 apneic unpreanesthetized cats after induction with alfaxalone. Other adverse reactions included hypotension, tachycardia, hypertension, bradypnea, bradycardia, and hypothermia (see ADVERSE REACTIONS).

In the field study, recovery times (extubation to head lift) following alfaxalone maintenance anesthesia averaged 15 minutes in cats that did not receive a preanesthetic, and 17 minutes in preanesthetized cats. Average recovery times following the use of an inhalant anesthetic ranged between 1-95 minutes (mean 14 minutes).

Dog field study: One hundred eighty-two dogs of 54 breeds, between the ages of 3 months to 13 years, weighing between 2.4 and 41 kg, were successfully anesthetized with alfaxalone (unpreserved) for various types of surgery or procedures requiring anesthesia. Induction doses ranged between 0.2 - 3.5 mg/kg for preanesthetized dogs, and between 1.5 - 4.5 mg/kg for dogs that did not receive a preanesthetic (see DOSAGE AND ADMINISTRATION for doses by preanesthetic treatment groups). The alfaxalone induction dose in the field study was reduced by 23-50% depending on the combination of preanesthetics (dose sparing effect). One hundred and eighteen dogs were maintained using an inhalant anesthetic; 17 dogs were maintained using between 1-5 alfaxalone boluses. Alfaxalone maintenance doses ranged between 1.2 - 1.4 mg/kg in preanesthetized dogs and 1.5 - 2.2 in unpreanesthetized dogs. Doses were given to effect and titrated against the response of the individual patient.

All dogs in the field study were intubated and received supplemental oxygen. Following induction using alfaxalone, apnea ≥30 seconds occurred in 46 (of 123) preanesthetized dogs and 9 (of 17) unpreanesthetized dogs. Apnea continued for ≥60 seconds in 18 of the 46 apneic preanesthetized dogs and 8 of the 9 apneic unpreanesthetized dogs after induction with alfaxalone. The duration of apnea ranged between 38 seconds and 6 minutes, 47 seconds. Of the 17 dogs that received up to 5 alfaxalone maintenance boluses, 11 (64.7%) experienced 14 periods of apnea, averaging 2.6 minutes each. Other adverse reactions included bradypnea, hypotension, tachycardia, hypertension, hypothermia, and bradycardia (see ADVERSE REACTIONS).

ANIMAL SAFETY

Plasma concentrations of alfaxalone over time after IV administration of ALFAXAN (unpreserved) or ALFAXAN MULTIDOSE to cats and dogs were compared and found to be bioequivalent for AUClast and Cmax (see CLINICAL PHARMACOLOGY). Monitoring of physiological variables, evaluation of anesthetic induction, anesthetic effectiveness, anesthetic recovery, and anesthetic event times during the bioequivalence study showed that the two formulations result in similar pharmacodynamic effects. The demonstrated blood level bioequivalence supports the systemic safety of the ALFAXAN MULTIDOSE formulation.

Cat multiple dose safety study: In a multiple dose safety study, 5 groups of 6 healthy cats (half male, half female) were administered ALFAXAN at 0 (saline), 5, 15 and 25 mg/kg on days 0, 2 and 5, at 48 hour intervals. Variables included induction and recovery times, heart rate (HR), respiratory rate (RR), indirect blood pressure (BP), clinical pathology, and necropsy. Anesthetic and cardiorespiratory variables were collected prior to induction and at 10 minute intervals after each induction until recumbence. Electrocardiograms (ECG) were monitored at observation time points.

Recovery time increased with increasing dose. Increasing doses of alfaxalone resulted in decreases in heart rate, respiratory rate, and blood pressure within 15 minutes postinduction. The lowest RR (18 breaths per minute) seen at 15 and 25 mg/kg occurred at 50 and 5 minutes post-dose respectively. Cats in the 5 mg/kg dose group reached a minimum of 23 breaths per minute at 10 minutes post-dose. During the initial 5 minutes after induction, there was 1 episode of apnea at 5 mg/kg, 6 episodes of apnea at 15 mg/kg, and 3 episodes of apnea at 25 mg/kg. Decreases in mean hemoglobin saturation (SpO2) were not dose related. The lowest mean hemoglobin concentration for cats in both the 5 and 15 mg/kg dose groups were approximately 88%. For cats that received 25 mg/kg, the lowest SpO2 was 83%. Mean systolic and diastolic blood pressure decreased with increasing dose. No abnormal cardiac arrhythmias were noted during the study (ECG observed but not recorded). Clinical pathology abnormalities were not clinically significant for all groups. Abnormal necropsy and histopathology findings were associated with injection site trauma consistent with intravenous injection and repeat catheterization. No pain on injection was reported.

The most common adverse reactions were post-anesthetic coughing, fluid in the endotracheal tube, and increased airway sounds. One death occurred in the 25 mg/kg group due to complications associated with a traumatic fall following extubation.

Cat preanesthetic compatibility study: Thirty healthy cats (15 female and 15 male cats) were allocated to each of 5 preanesthetic treatment groups. Alfaxalone dose sparing and the cardiovascular and respiratory interaction of alfaxalone when administered following intramuscular preanesthetic administration of acepromazine, medetomidine, midazolam, butorphanol, or saline, were evaluated. No procedures were performed; no cat received maintenance anesthesia.

Preanesthetic, preanesthetic dose, alfaxalone dose, and duration of anesthesia
Preanesthetic (IM) | Preanesthetic Dose | Alfaxalone IV Induction Dose (mg/kg) | Average Duration of Anesthesia (min)
medetomidine | 100 mcg/kg | 2.2 | 98.2
acepromazine | 1.1 mg/kg | 2.7 | 36.3
butorphanol | 0.4 mg/kg | 2.8 | 26.5
0.9% saline | 0 mg/kg | 3.0 | 26.1
midazolam | 0.1 mg/kg | 3.3 | 16.7

Cats given midazolam as the sole preanesthetic required more alfaxalone than the saline group. Durations of recovery increased with the duration of anesthesia. Physiologic variables (HR, RR, BP, SpO2) remained satisfactory during anesthesia and reflected the effects primarily of the associated preanesthetic. Transient cardiac arrhythmias were noted during alfaxalone anesthesia in several cats. Three cats preanesthetized with medetomidine experienced sinus arrhythmias (1 prior to alfaxalone) and 3 were bradycardic (HR <110 bpm). Two cats that received midazolam preanesthesia showed isolated ventricular premature contractions (VPC; 1 prior to alfaxalone).

The quality of anesthesia based on overall anesthetic scores was acceptable for all groups. However, the quality of midazolam preanesthesia, when used alone prior to alfaxalone anesthesia, was less satisfactory compared with other preanesthetics.

Cat tolerance safety study: Eight adult, healthy cats (4 male and 4 female) received 0 (saline), 5, 15, and 50 mg/kg of alfaxalone over 2 days in a dose escalation design, with at least 3 hours between doses.

Decreases in HR, RR, decreases in PaO2, and increases in PaCO2 were related to dose. All cardiopulmonary variables returned to baseline values by 15 minutes (5 mg/kg), 30 minutes (15 mg/kg) and 1 hour (50 mg/kg) after alfaxalone administration. The 50 mg/kg dose produced marked cardiovascular depression lasting from 10 to 30 minutes. Five of seven cats dosed at 50 mg/kg were euthanised due to prolonged hypoxia after 5 hours of anesthesia.

Apnea occurred at all doses. Respiratory depression and apnea (duration averaging 21 seconds, 63 seconds and 28 minutes) were observed at the 5, 15 and 50 mg/ kg doses, respectively. The duration of apnea generally increased with the alfaxalone dose, occurring more often and for longer duration at 15 and 50 mg/kg. One cat experienced apnea lasting 3 minutes at 5 mg/kg. Tracheal intubation and administration of 100% oxygen and manual artificial ventilation were needed to raise arterial PaO2 from < 60 mm Hg to > 80 mm Hg. Five cats received oxygen at 5 mg/kg, 7 received oxygen at 15 mg/kg, and all cats required oxygen at 50 mg/kg. Other adverse reactions at 5 mg/kg included 1 cat with cyanotic mucous membranes, and 1 cat with fluid in the endotracheal tube.

Duration of anesthesia increased with higher doses, lasting 26, 83, and 126 minutes after administration of 5, 15, and 50 mg/kg, respectively. Average quality scores (1, 2 or 3 - with 1 being the best) for induction and anesthesia were 1 for cats that received the 5 or 15 mg/kg doses. Average quality scores for recovery were 1 and 1.1 for the 5 and 15 mg/kg groups, respectively.

Dog multiple dose safety study: In a multiple dose safety study, 4 groups of 6 healthy Beagle dogs (3 male, 3 female) were administered alfaxalone (unpreserved) at 0 (saline), 2, 6, and 10 mg/kg, 3 times at 48 hour intervals. Variables included induction and recovery times, HR, RR, indirect BP, clinical pathology, urinalysis, and necropsy. Anesthetic and cardiorespiratory variables were collected prior to induction and at 10 minute intervals after each induction until recumbency. Health observations, clinical pathology, and urinalysis variables were collected during the study on non-treatment days.

Induction times decreased and recovery times increased with relation to the anesthetic dose. Body temperature decreased in proportion to the dose and the length of anesthesia. The minimum rectal temperature recorded was 98.3°F. There was a dose related decrease in SpO2, respiratory rate, and blood pressures. Mean heart rates increased with the increase in alfaxalone dosage. Mean heart rates also increased when compared to the pre-dose heart rate at the 10-minute time point for all groups. Heart rates returned to pre-dose rates or below at the 20 minute time points for the 2mg/kg and 6mg/kg groups, and at the 30 minute time point for the 10mg/kg group. There was a decrease in the mean respiratory rates for all treatment groups when compared to the pre-dose rate, lowest at the 10 minutes time point. Mean systolic BP decreased and was lowest in all groups at the 10 minute time point for the 2mg/kg dogs, and at the 20 minute time point for 6mg/kg and 10mg/kg groups. Similar trends were recorded for diastolic BP and MAP. Clinical pathology abnormalities were not clinically significant in all groups; abnormal necropsy and histopathology findings were associated with injection site trauma consistent with intravenous injection and repeat catheterization. No pain on injection was reported. No abnormal cardiac arrhythmias were noted during the study (ECG observed but not recorded).

Dog preanesthetic compatibility study: Forty eight healthy Beagle dogs (24 males, 24 females) were enrolled with 3 females and 3 males allocated to each of 8 preanesthetic groups (0.9% saline, medetomidine 40µg/kg, medetomidine 4µg/kg, acepromazine 1.1 mg/kg, acepromazine 0.2 mg/kg, acepromazine 0.05 mg/kg, butorphanol 0.2 mg/kg, and midazolam 0.2 mg/kg). All treatment groups received a maximum induction dose of 2 mg/kg of alfaxalone (to achieve endotracheal intubation) in conjunction with an intravenous dose of differing preanesthetic according to treatment group. No procedure was performed. Data were collected on each dog for the quality of anesthesia, as well as cardiovascular and respiratory parameters. Data for the cardiovascular and respiratory variables were collected between preanesthetic administration until recovery at intervals of -60, -5, 5, 10, 15, and 20 minutes and every 10 minutes thereafter.

Dose sparing occurred with acepromazine, medetomidine, and butorphanol. Dogs administered midazolam required an increase in dose compared to the saline group.The high medetomidine and 1.1 mg/kg acepromazine groups had the largest dose sparing effect on alfaxalone. The 0.2 mg/kg and 1.1 mg/kg acepromazine, low dose medetomidine, midazolam, and butorphanol groups had mean durations of anesthesia between 7:58 and 10:17 min/sec. The high medetomidine group had a prolonged mean duration of anesthesia at 1:10:08 (hr/min/sec). Duration of recovery increased with the duration of anesthesia. Midazolam treated dogs had the least satisfactory recovery scores.

No dog experienced hypotension. Mean heart rates decreased compared to baseline values. Dogs in the high medetomidine group experienced bradycardia through the end of anesthesia. Heart rates for the saline, 0.05 mg/kg acepromazine, and midazolam groups increased between the -5 minutes and 5-minute time points. The midazolam group experienced mean heart rates of 170-175 at the 5-10 minute time points. Dogs in the 0.2 mg/kg and 1.1 mg/kg acepromazine group, and butorphanol group had stable heart rates from baseline, premedication, and through anesthesia. Electrocardiogram recordings were evaluated by the study investigator, and no abnormal findings were noted. Blood pressures were obtained by an indirect method and remained normal in all groups throughout anesthesia. Respiratory rates decreased in the high and low medetomidine groups after premedication (-5 minutes) and again after alfaxalone administration (5 minutes). Decreases for the other groups occurred after alfaxalone administration, and had not returned to baseline values at the last recorded time point. No apnea was observed.

Dog tolerance safety study: Eight dogs (4 male, 4 female) each received 0 (0.9% saline), 2, 6, and 20 mg/kg of alfaxalone (unpreserved) in sequence, with a 3 hour washout period between doses. There were no unscheduled deaths during the study. Necropsy and histopathology were not conducted. Alfaxalone produced dose related decreases in cardiovascular, respiratory, pH, and blood gas values, and dose related increases for duration of anesthesia, time to extubation, and time to sternal recumbency. There were no ECG abnormalities reported during the study. Observations during anesthesia included forelimb rigidity and shivering/shaking during recovery, paddling, excitement during recovery, inability to intubate (1X).

Apnea occurred in a dose dependent manner, and all dogs required oxygen supplementation and positive pressure ventilation after administration of the 20mg/kg dose. One dog experienced apnea after administration of the 2mg/kg dose, and 6 dogs experienced apnea after the 6mg/kg dose. These dogs did not require oxygen supplementation. The mean duration of apnea also increased in a dose related manner. Decreases in respiratory rate were most profound at 1 through 10 minutes in the 6mg/kg group, and 1 through 30 minutes in the 20mg/kg group. Tidal volume and minute volume decreased in a dose dependent manner, along with the respiratory rate.

Blood pressures were obtained from an arterial catheter. At all doses, there was an increase in the mean heart rate, compared to baseline values. At the 20mg/kg dose, the heart rate returned to near baseline values between the 5 and 15 minute time points. At 20mg/kg, the heart rates were tachycardic (means 155-168 bpm); at the 2mg/kg and 6mg/kg doses the heart rates were elevated (means 143-150 bpm). At the 2mg/kg and 6mg/kg doses, the MAP and systolic BP increased compared to baseline, and at the 20mg/kg dose, the MAP and systolic BP decreased compared to baseline. These changes occurred at 1 and 5 minutes at the 2mg/kg dose, and at 1 minute for the 6mg/kg dose. The mean MAP and systolic BP returned to baseline values by the end of anesthesia. Cardiac output (CO) and central venous pressure (CVP) were lowest in the 20mg/kg group at 5 and 30 minutes.

Dog cesarean section safety study: Forty-eight female dogs received alfaxalone (unpreserved) for induction prior to cesarean section, and were maintained using isoflurane. The average induction dose of alfaxalone was 1.9 mg/kg. Immediate, transient, post-induction apnea occurred in 15% of cases. Cardiovascular and respiratory parameters were well maintained during induction, maintenance and recovery, and anesthesia quality was scored as good during all phases. Puppy vigor scores were rated as very good for withdrawal reflex, sucking reflex, anogenital reflex, and flexion reflex. Puppy survival rate was 96.2% at 24 hours after birth.

STORAGE INFORMATION

Store at controlled room temperature 20°C - 25°C (68° to 77°F) with excursions between 15° and 30°C (59° and 86°F). ALFAXAN MULTIDOSE contains preservatives. The product can be used for 56 days after broaching the vial. Any unused ALFAXAN MULTIDOSE remaining after 56 days should be discarded.

HOW SUPPLIED

ALFAXAN MULTIDOSE is supplied in 10 and 20 mL multiple-dose vials containing 10 mg alfaxalone per mL.

ALFAXAN is a registered trademark of Jurox Pty Ltd.
Approved by FDA under NADA # 141-342
Manufactured in Australia by Jurox Pty Ltd.
Distributed by:
Zoetis Inc.
Kalamazoo, MI 49007
Revised: April 2023
471610

PRINCIPAL DISPLAY PANEL - 10 mL Carton

471615

PRINCIPAL DISPLAY PANEL - 20 mL Carton

471630